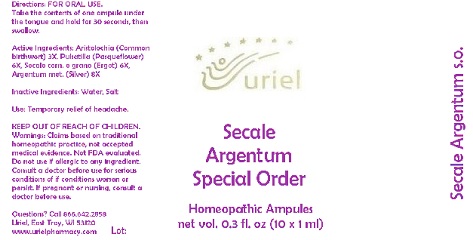 DRUG LABEL: Secale Argentum Special Order
NDC: 48951-8172 | Form: LIQUID
Manufacturer: Uriel Pharmacy Inc.
Category: homeopathic | Type: HUMAN OTC DRUG LABEL
Date: 20180524

ACTIVE INGREDIENTS: ARISTOLOCHIA CLEMATITIS WHOLE 3 [hp_X]/1 mL; PULSATILLA VULGARIS 6 [hp_X]/1 mL; CLAVICEPS PURPUREA SCLEROTIUM 6 [hp_X]/1 mL; SILVER 8 [hp_X]/1 mL
INACTIVE INGREDIENTS: WATER; SODIUM CHLORIDE

Secale Argentum Special Order

INDICATIONS AND USAGE

Directions: FOR ORAL USE.

DOSAGE AND ADMINISTRATION

Take the contents of one ampule under the tongue and hold for 30 seconds, then swallow.

ACTIVE INGREDIENT

Active Ingredients: Aristolochia ex herba 3X, Pulsatilla e flor. 6X, Secale corn. e grano 6X, Argentum metallicum 8X

Inactive Ingredients: Water, Salt

PURPOSE

Use: Temporary relief of headache.

KEEP OUT OF REACH OF CHILDREN.

WARNINGS

Warnings: Claims based on traditional homeopathic practice, not accepted medical evidence. Not FDA evaluated. Do not use if allergic to any ingredient. Consult a doctor before use for serious conditions of if conditions worsen or persist. If pregnant or nursing, consult a doctor before use.